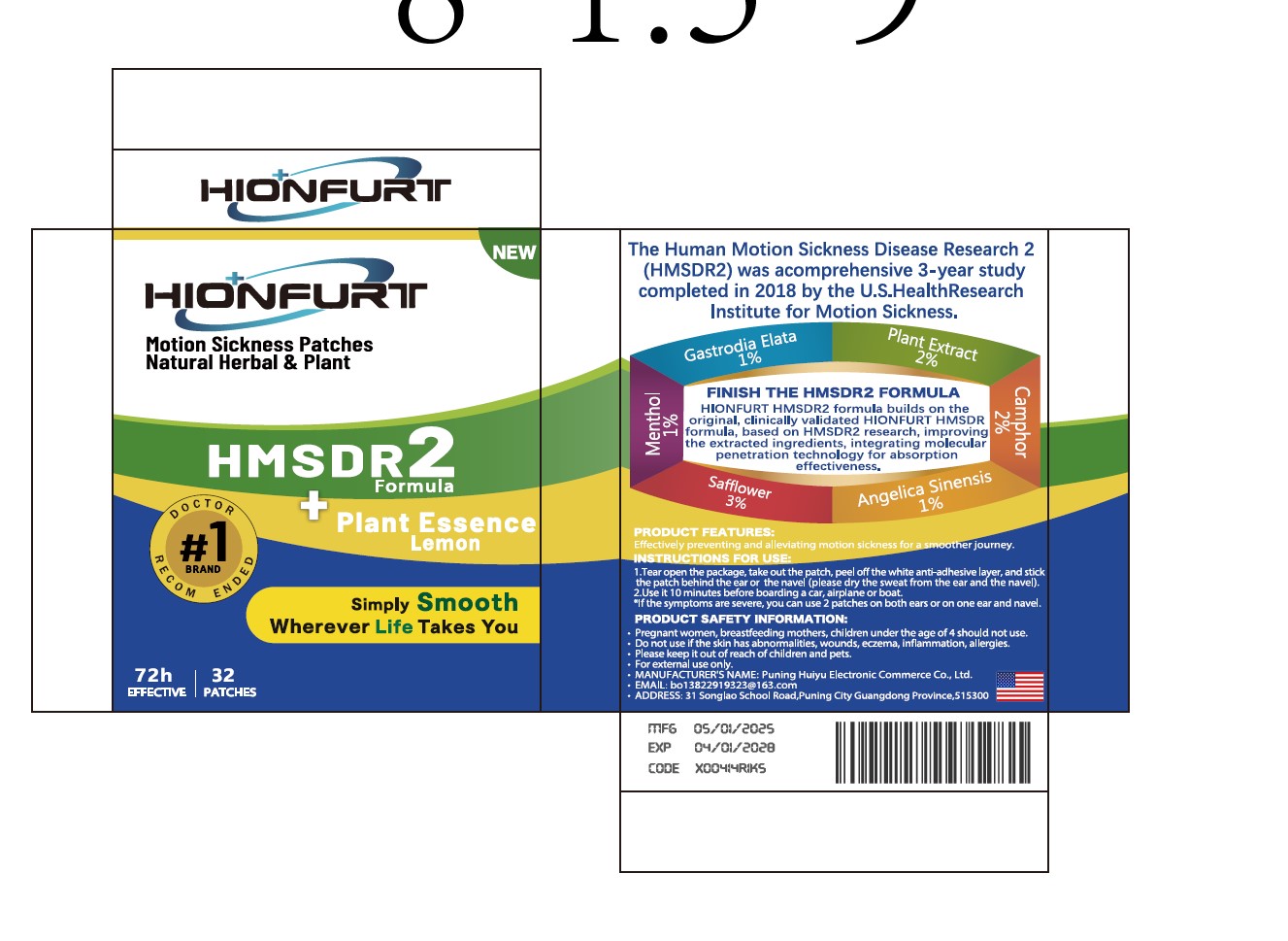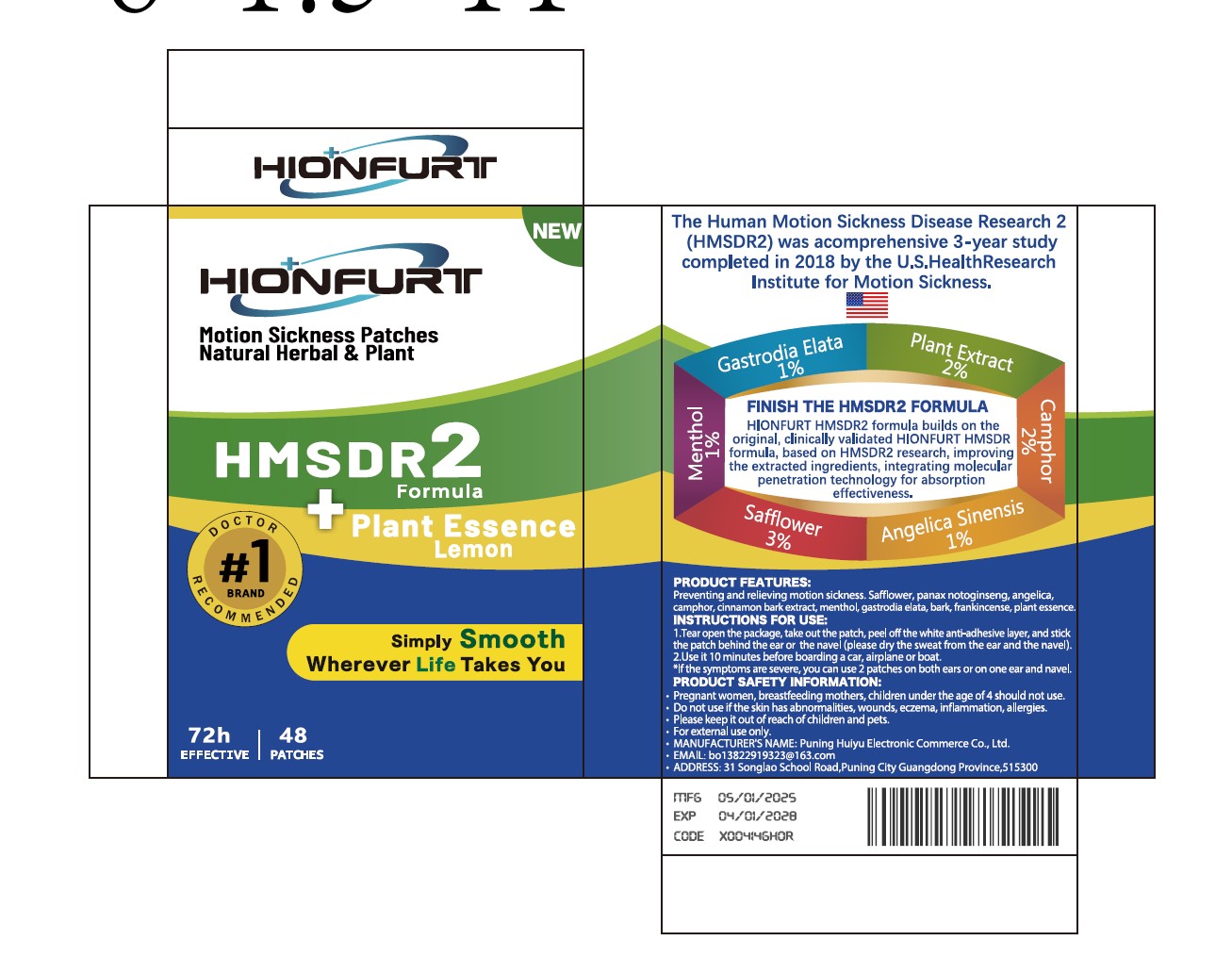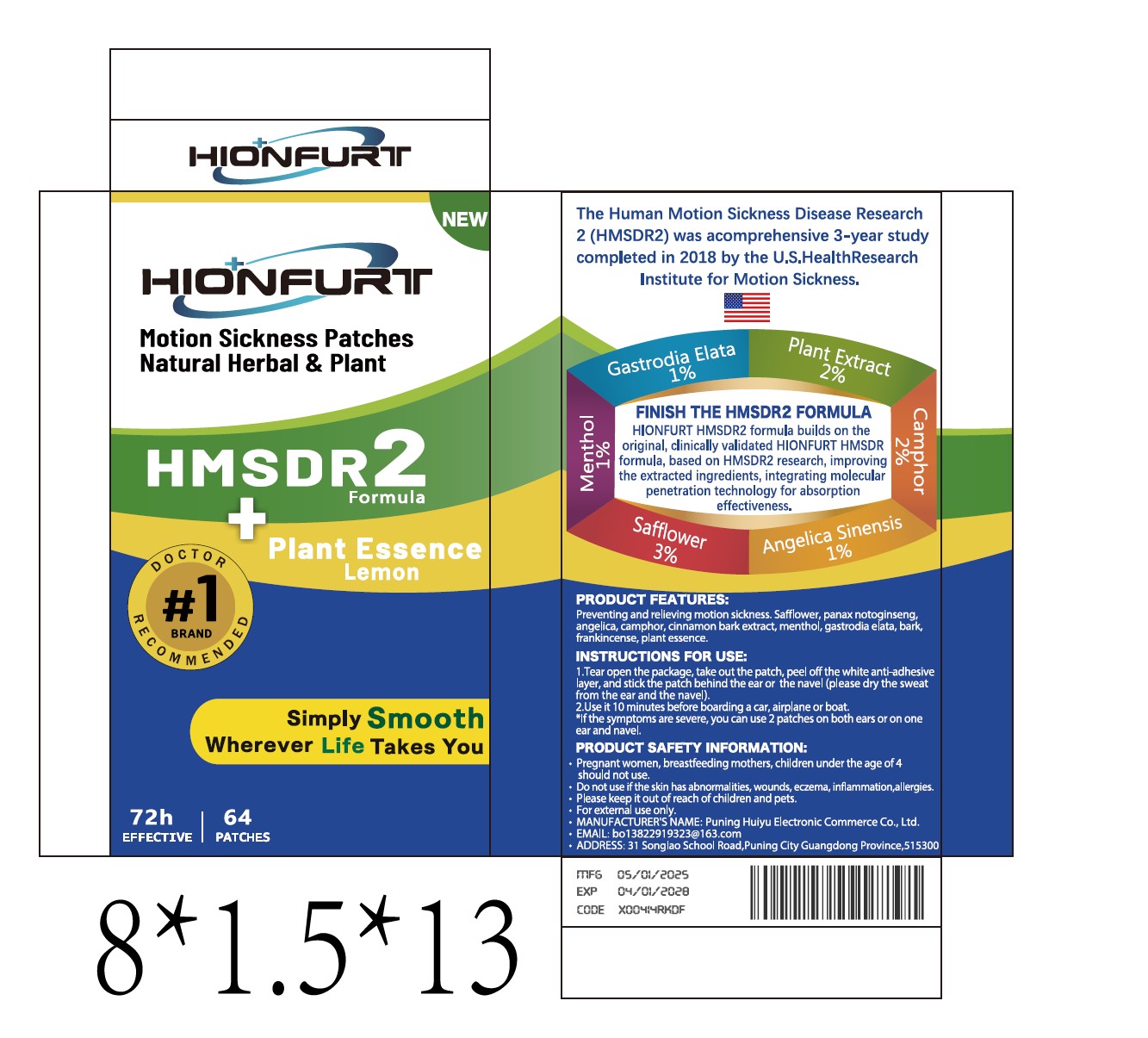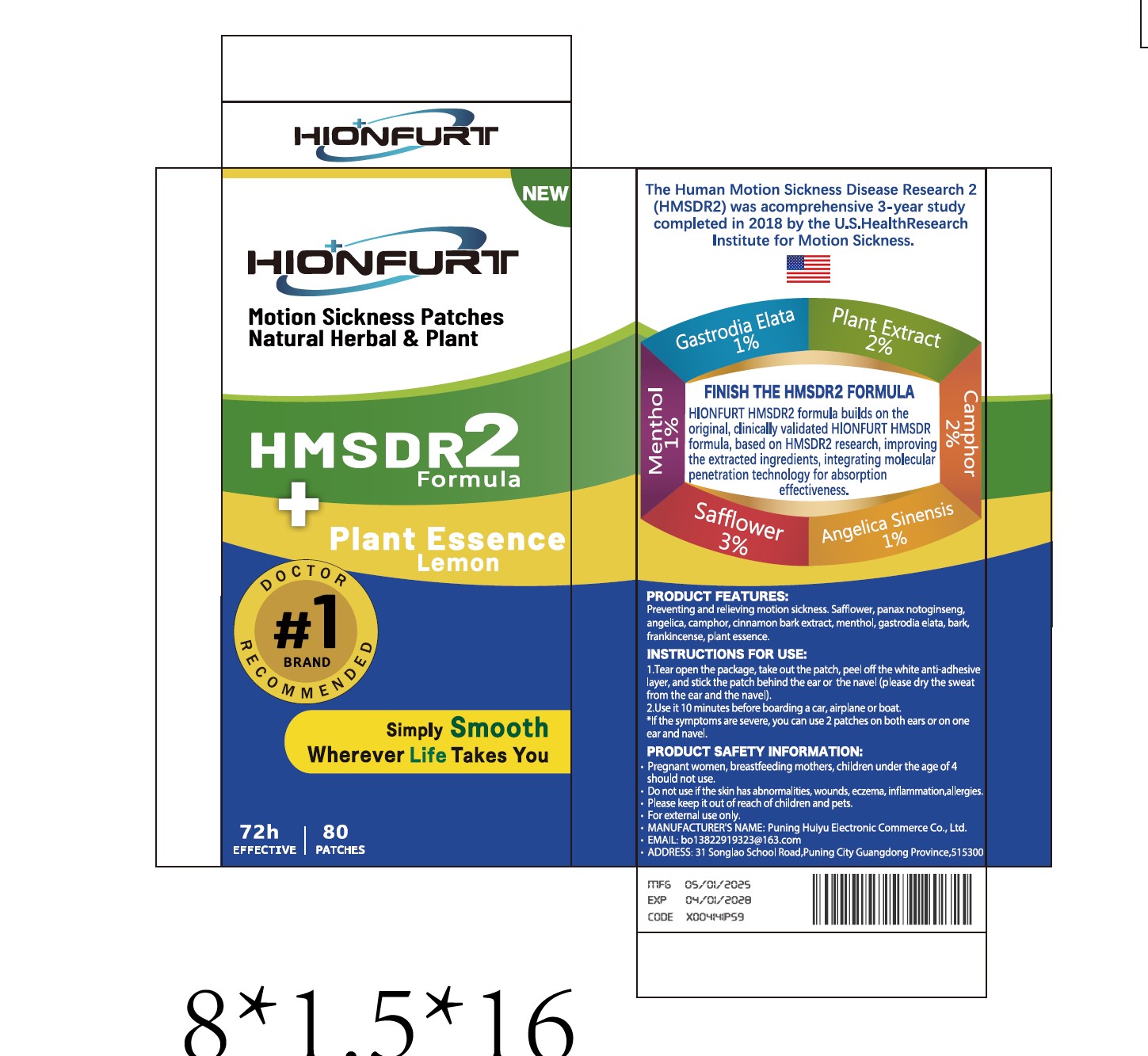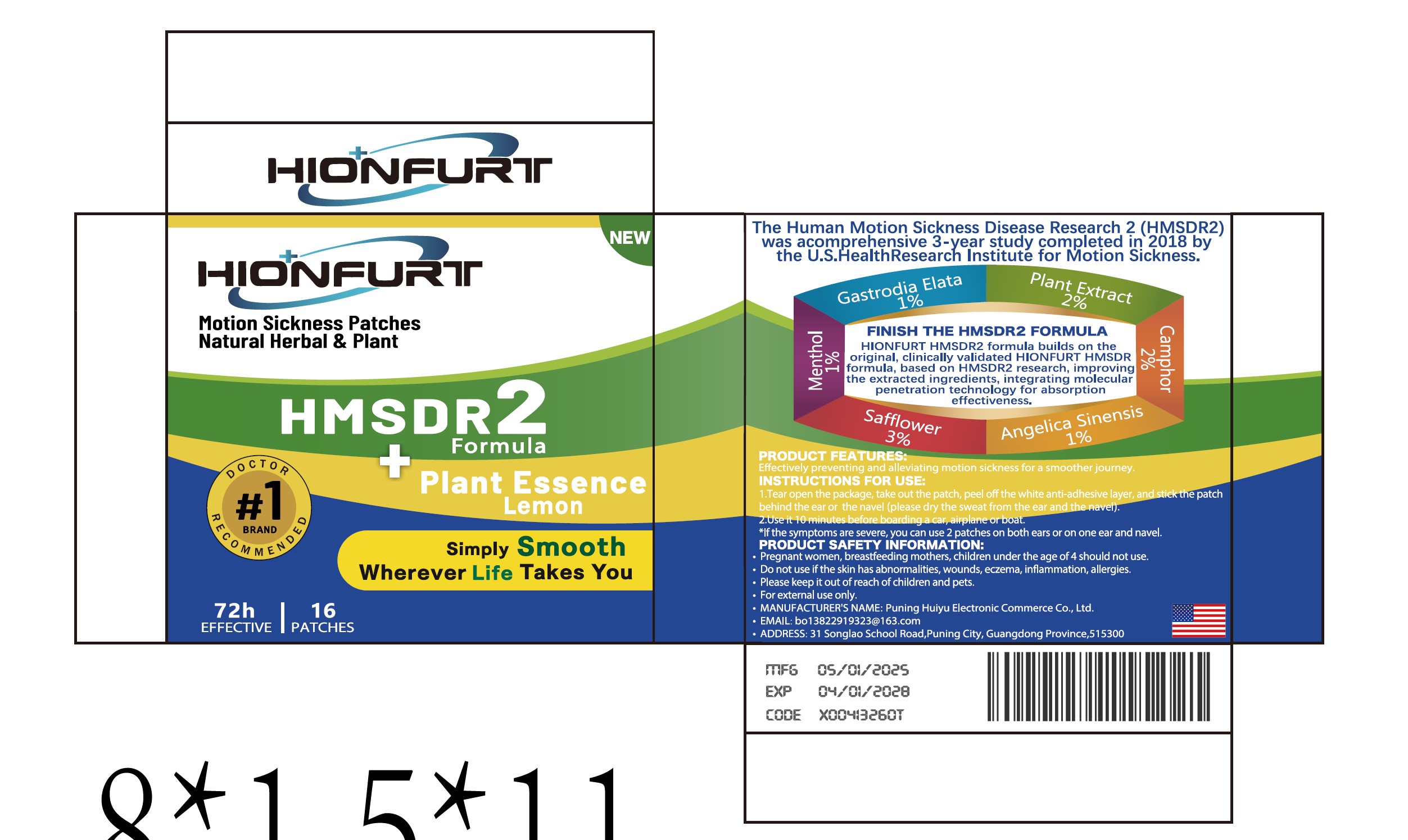 DRUG LABEL: HIONFURT Motion Sickness
NDC: 85213-002 | Form: PATCH
Manufacturer: Puning Huiyu E-Commerce Co., Ltd.
Category: otc | Type: HUMAN OTC DRUG LABEL
Date: 20250215

ACTIVE INGREDIENTS: MENTHOL GLUCURONIDE 10 mg/100 g; CAMPHOR, (-)- 20 mg/100 g
INACTIVE INGREDIENTS: EGGPLANT; GASTRODIA ELATA WHOLE; ANGELICA SINENSIS WHOLE; SAFFLOWER

Active ingredient

Menthol , Camphor

INACTIVE INGREDIENT

Plant Extract
Gastrodia Elata
Safflower
Angelica Sinensis

PURPOSE

PRODUCT FEATURES:
Effectively preventing and alleviating motion sickness for a smoother journey

When using this product

lf the symptoms are severe, you can use 2 patches on both ears or on one ear and
navel

Do not use

Pregnant women, breastfeeding mothers, children under the age of4 should not use.Do
not use if the skin has abnormalities, wounds, eczema, inflammation, allergies.Please
keep it out of reach of children and pets.

keep out of children

Please keep it out of reach of children and pets.
For external use only.

Dosage

Use it 10 minutes before boarding a car, airplane or boat.*lf the symptoms are severe,
you can use 2 patches on both ears or on one ear and navel

warning

Pregnant women, breastfeeding mothers,
children under the age of 4 should not use
.Do not use if the skin has abnormalities, wounds, eczema, inflammation, allergies.
Please keep it out of reach of children and pets.
For external use only.

Indications

1.Tear open the package, take out the patch, peel off the white anti-adhesive layer, and
stick the patchbehind the ear or the navel (please dry the sweat from the ear and the
navel).
2.Use it 10 minutes before boarding a car, airplane or boat.*lf the symptoms are severe,
you can use 2 patches on both ears or on one ear and navel